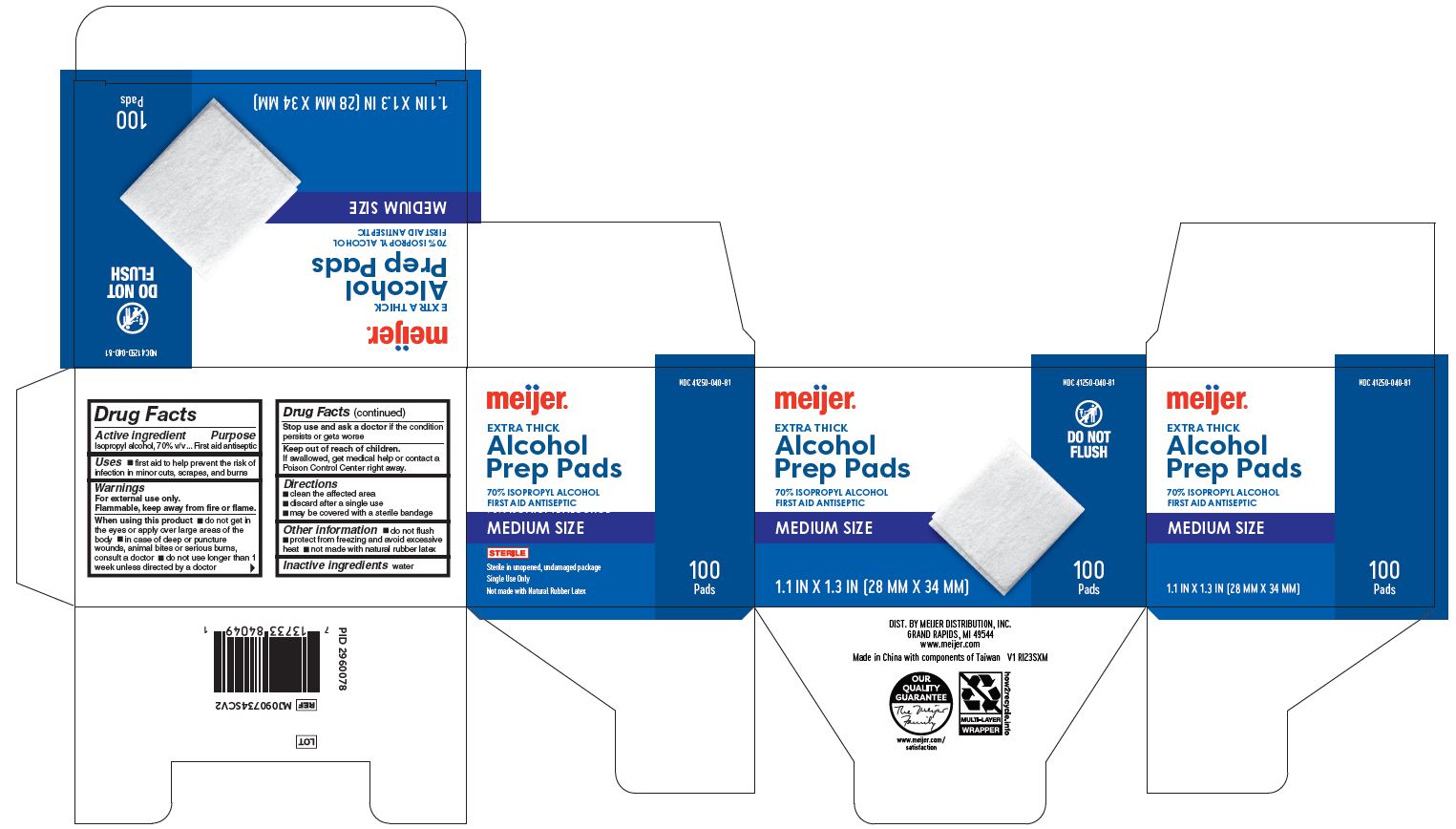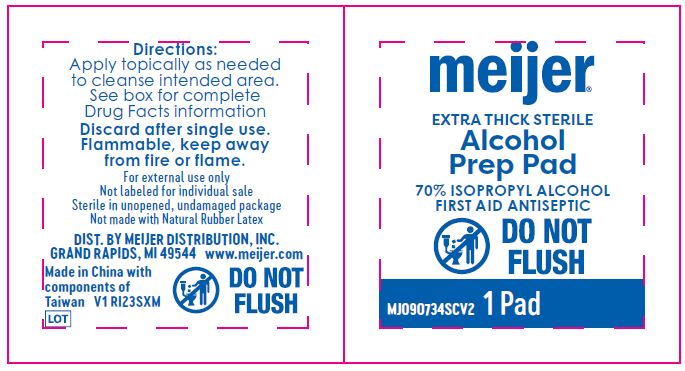 DRUG LABEL: Alcohol
NDC: 41250-040 | Form: SWAB
Manufacturer: Meijer Distribution Inc
Category: otc | Type: HUMAN OTC DRUG LABEL
Date: 20250103

ACTIVE INGREDIENTS: ISOPROPYL ALCOHOL 70 mL/100 mL
INACTIVE INGREDIENTS: WATER

41250-040 Meijer IPA Pad

Active ingredient

Isopropyl alcohol 70% v/v

Purpose

First aid antiseptic

Uses

- • first aid antiseptic to help prevent infection in minor cuts, scrapes and burns

Warnings

- For external use only.
- Flammable, keep away from fire or flame.

Do not use

- • with electrocautery procedures
- • longer than 1 week unless directed by a doctor

When using this product

- • do not get into eyes
- • do not apply over large areas of the body
- • in case of deep or puncture wounds, animal bites or serious burns, consult a doctor

Stop use and ask a doctor if

- • irritation and redness develop
- • condition persists or gets worse or lasts for more than 72 hours

Keep out of reach of children.

If accidentally swallowed, get medical help or contact a Poison Control Center right away.

Directions

- clean the affected area
- discard after single use
- may be covered with a sterile bandage

Other information

- • protect from freezing and avoid excessive heat
- • not made with natural rubber latex

Inactive ingredients

water

Manufacturing information

Distributed by:

Meijer Distribution, Inc.

2929 Walker Ave NW, Grand Rapids, MI 49544 USA

Made in China with componets from Taiwan

www.meijer.com

REF: MJ090734SCV2

V1 RI23SXM